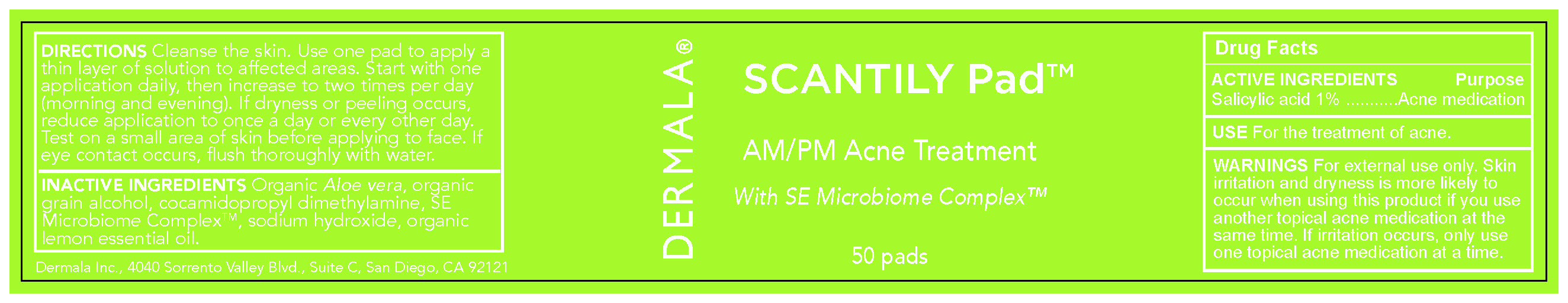 DRUG LABEL: Scantily Pad
NDC: 65112-268 | Form: LIQUID
Manufacturer: I Shay Cosmetics Inc
Category: otc | Type: HUMAN OTC DRUG LABEL
Date: 20211203

ACTIVE INGREDIENTS: SALICYLIC ACID 0.01 mg/1 mg
INACTIVE INGREDIENTS: WATER 0.8 mg/1 mg

Dermala Acne Treatment

Use

For the treatment of Acne.

Active Ingredient

Salicylic acid 1% ...........Acne Treatment

Warning

WARNINGS For external use only. Skin irritation and dryness is more likely to occur when using this product if you use another topical acne medication at the same time. If irritation occurs, only use one topical acne medication at a time.

Incative ingredients

INACTIVE INGREDIENTS Organic Aloe vera, organic grain alcohol, cocamidopropyl dimethylamine, SE Microbiome ComplexTM, sodium hydroxide, organic lemon essential oil.

DOSAGE AND ADMINISTRATION

DIRECTIONS Cleanse the skin. Use one pad to apply a thin layer of solution to affected areas. Start with one application daily, then increase to two times per day (morning and evening). If dryness or peeling occurs, reduce application to once a day or every other day. Test on a small area of skin before applying to face. If eye contact occurs, flush thoroughly with water.

children

keep out of reach of children

indications and usage

For the treatment of Acne